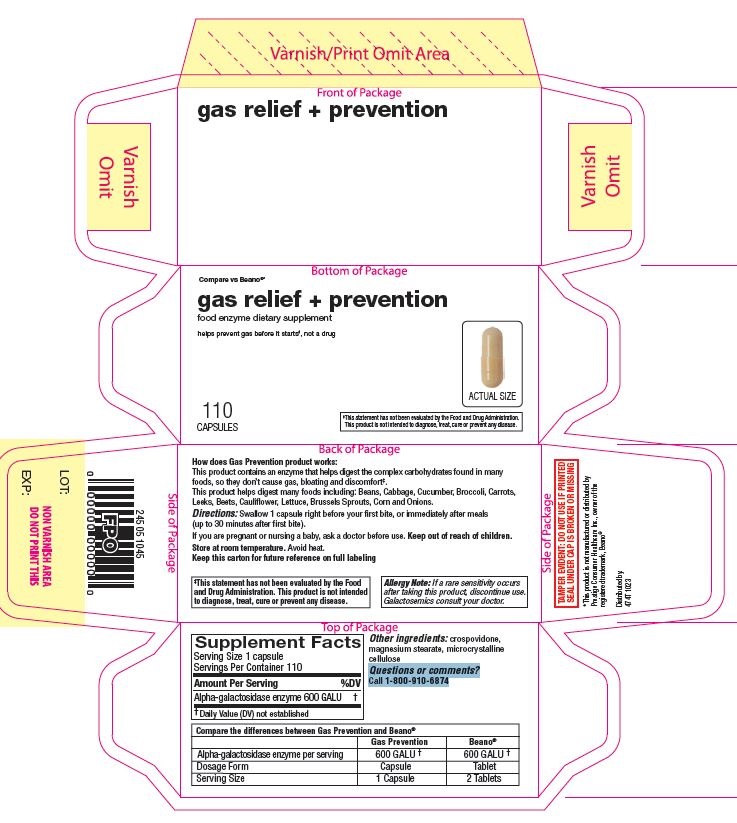 DRUG LABEL: Alpha Galactosidase
NDC: 11673-883 | Form: CAPSULE
Manufacturer: TARGET CORPORATION
Category: other | Type: Dietary Supplement
Date: 20240901

ACTIVE INGREDIENTS: AGALSIDASE ALFA 600 umol/1 1
INACTIVE INGREDIENTS: CROSPOVIDONE; MAGNESIUM STEARATE; MICROCRYSTALLINE CELLULOSE

Alpha Galactosidase Enzyme Capsules

STATEMENT OF IDENTITY

ALPHA GALACTOSIDASE

Directions

Directions: Swallow 1 capsule right before your first bite, or immediately after meals (up to 30 minutes after first bite).

Supplement Facts

Serving Size 1 capsule

Servings Per Container 110

Amount Per Serving

%DV

Alpha-galactosidase enzyme 600 GALU

†

†Daily Value (DV) not established

Compare the differences between Gas Prevention and Beano®
 | Gas Prevention | Beano®
Alpha-galactosidase enzyme per serving | 600 GALU | 600 GALU
Dosage Form | Capsule | Tablet
Serving Size | 1 Capsule | 2 Tablets

Warnings

If you are pregnant or nursing a baby, ask a doctor before use. Keep out of reach of children.

Store at room temperature. Avoid heat.
Keep this carton for future reference on full labeling

‡This statement has not been evaluated by the Food and Drug Administration. This product is not intended to diagnose, treat, cure or prevent any disease.

Allergy Note: If a rare sensitivity occurs after taking this product, discontinue use. Galactosemics consult your doctor.

Other ingredients: crospovidone, magnesium stearate, microcrystalline cellulose

Questions or comments? Call 1-800-910-6874

How does Gas Prevention product works:

This product contains an enzyme that helps digest the complex carbohydrates found in many
foods, so they don’t cause gas, bloating and discomfort‡.
This product helps digest many foods including: Beans, Cabbage, Cucumber, Broccoli, Carrots,
Leeks, Beets, Cauliflower, Lettuce, Brussels Sprouts, Corn and Onions.

474T-Alphagalacto-110ct-carton

PACKAGE LABEL

474T-Alphagalacto-110ct-carton